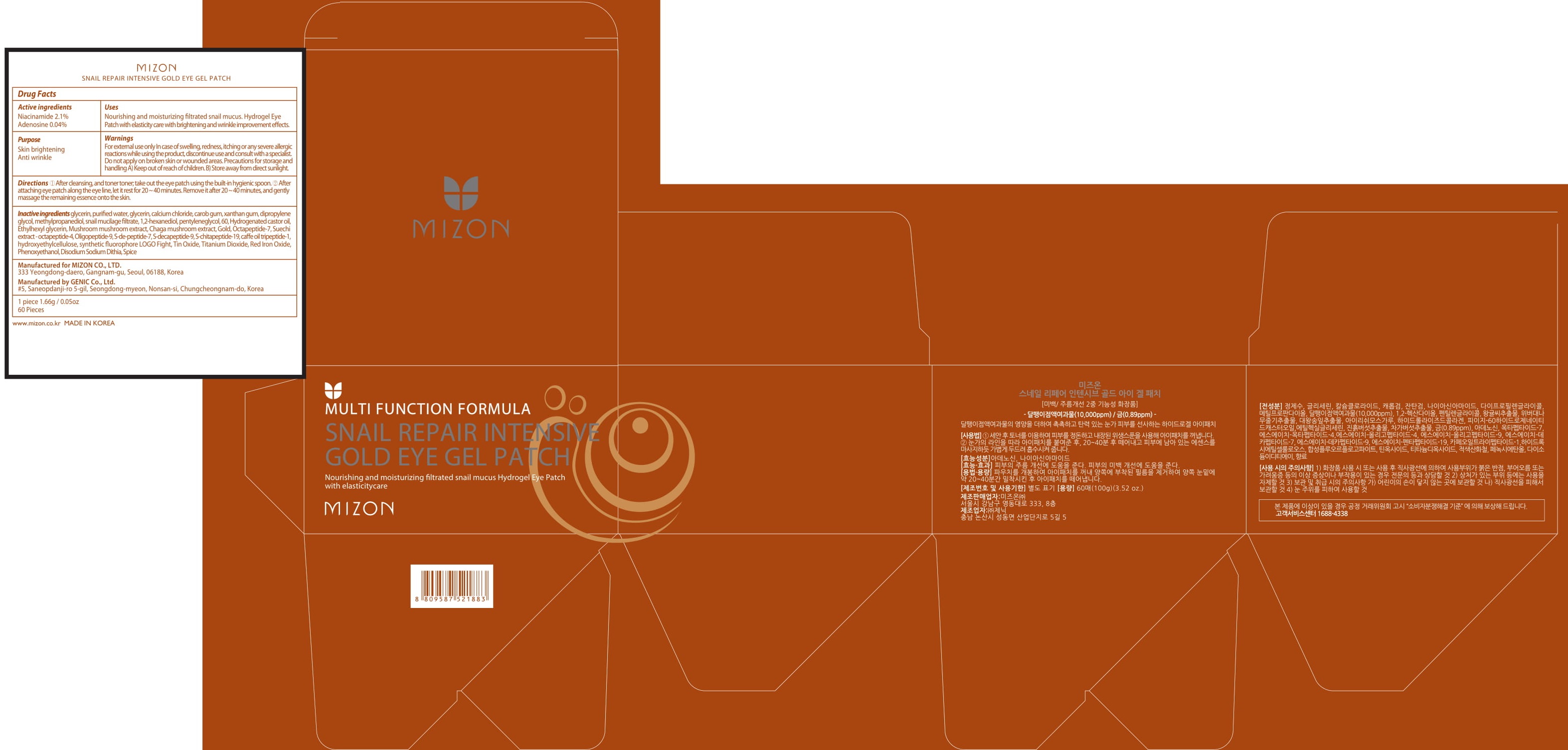 DRUG LABEL: MIZON SNAIL REPAIR INTENSIVE GOLD EYE GE L
NDC: 57718-380 | Form: PATCH
Manufacturer: MIZON CO.,LTD.
Category: otc | Type: HUMAN OTC DRUG LABEL
Date: 20191230

ACTIVE INGREDIENTS: Niacinamide 0.034 g/1.66 g; Adenosine 0.0006 g/1.66 g
INACTIVE INGREDIENTS: glycerin; water

ACTIVE INGREDIENT

Active ingredients: Niacinamide 2.1%, Adenosine 0.04%

INACTIVE INGREDIENT

Inactive ingredients:

glycerin, purified water, glycerin, calcium chloride, carob gum, xanthan gum, dipropylene glycol, methylpropanediol, snail mucilage filtrate, 1,2-hexanediol, pentyleneglycol, 60, Hydrogenated castor oil, Ethylhexyl glycerin, Mushroom mushroom extract, Chaga mushroom extract, Gold, Octapeptide-7, Suechi extract - octapeptide-4, Oligopeptide-9, S-de-peptide-7, S-decapeptide-9, S-chitapeptide-19, caffe oil tripeptide-1, hydroxyethylcellulose, synthetic fluorophore LOGO Fight, Tin Oxide, Titanium Dioxide, Red Iron Oxide, Phenoxyethanol, Disodium Sodium Dithia, Spice

PURPOSE

Purpose: Skin brightening, Anti wrinkle

WARNINGS

For external use only

In case of swelling, redness, itching or any severe allergic reactions while using the product, discontinue use and consult with a specialist.

Do not apply on broken skin or wounded areas.

Precautions for storage and handling

A) Keep out of reach of children.

B) Store away from direct sunlight.

KEEP OUT OF REACH OF CHILDREN

Uses

Nourishing and moisturizing filtrated snail mucus. Hydrogel Eye Patch with elasticity care with brightening and wrinkle improvement effects.

Directions

1) After cleansing, and toner toner; take out the eye patch using the built-in hygienic spoon.

2) After attaching eye patch along the eye line, let it rest for 20 ~ 40 minutes. Remove it after 20 ~ 40 minutes, and gently massage the remaining essence onto the skin.